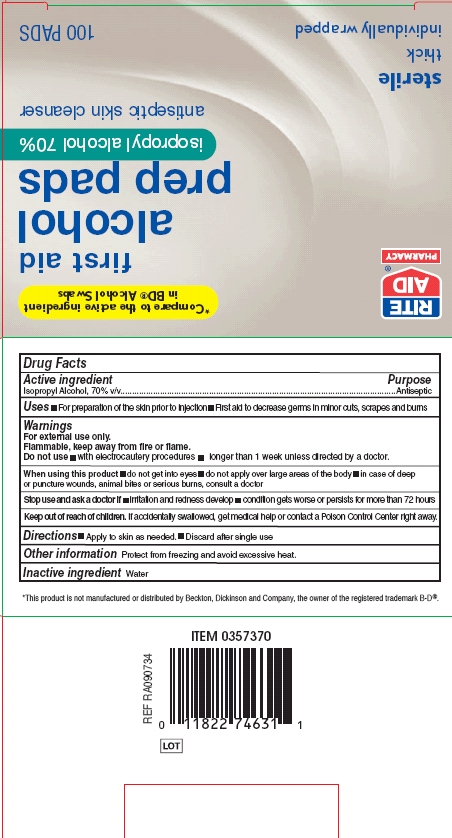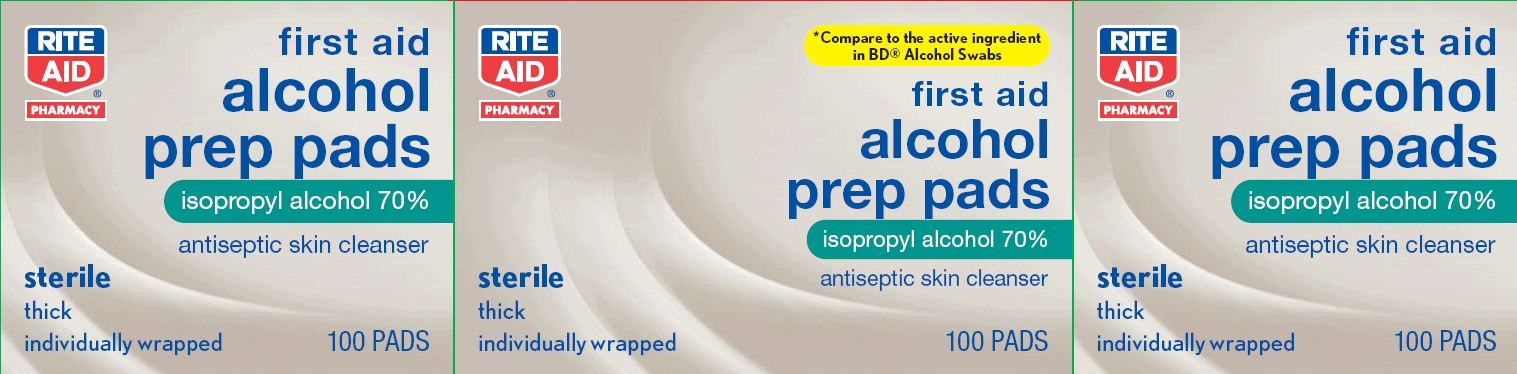 DRUG LABEL: Alcohol
NDC: 11822-7463 | Form: SWAB
Manufacturer: Rite Aid Corporation
Category: otc | Type: HUMAN OTC DRUG LABEL
Date: 20131226

ACTIVE INGREDIENTS: ISOPROPYL ALCOHOL 70 mL/100 mL
INACTIVE INGREDIENTS: WATER

Drug Facts

Active ingredient

Isopropyl alcohol, 70% w/v

Purpose

Antiseptic

Uses

- For preparation of the skin prior to injection
- First aid to decrease germs in minor cuts, scrapes and burns

Warnings

For external use only.

Flammable, keep away from fire or flame.

Do not use

- with electrocautery procedures
- longer than 1 week unless directed by a doctor

When using this product

- do not get into eyes
- do not apply over large areas of the body
- in case of deep or puncture wounds, animal bites or serious burns, consult a doctor
- use only in well ventilated area; fumes may be toxic

Stop use and ask a doctor if

- irritation or redness develop
- condition gets worse or persists for more than 72 hours

Keep out of reach of children.

If accidentally swallowed, get medical help or contact a Poison Control Center right away.

Directions

- Apply to skin as needed.
- Discard after single use

Other information

Protect from freezing and avoid excessive heat.

Inactive ingredients

Water

Package/Label Principal Display Panel

Rite Aid Pharmacy

Compare to the active ingredient in BD® Alcohol Swabs

first aid

Alcohol Prep Pads

isopropyl alcohol 70%

antiseptic skin cleanser

sterile

thick

individually wrapped

100 PADS